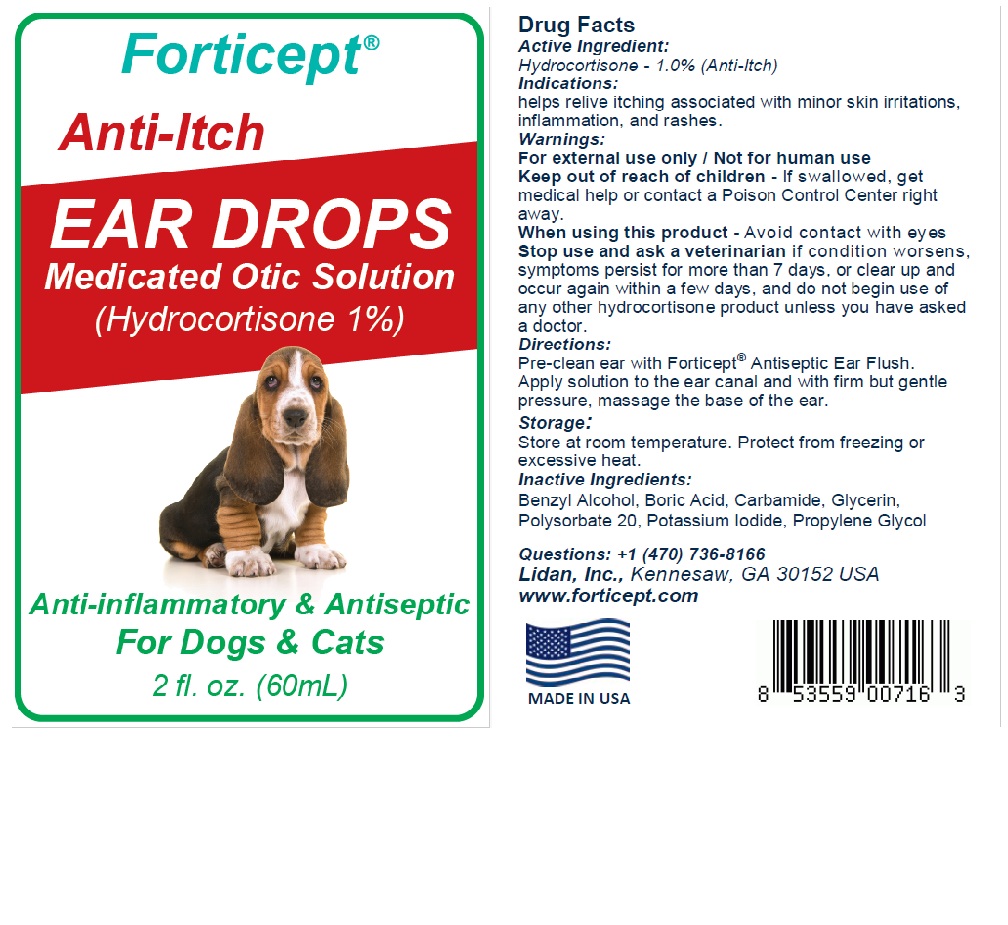 DRUG LABEL: Forticept Anti-Itch Ear Drops
NDC: 72127-0906 | Form: LIQUID
Manufacturer: Lidan, Inc.
Category: animal | Type: OTC ANIMAL DRUG LABEL
Date: 20251107

ACTIVE INGREDIENTS: HYDROCORTISONE 10 g/1000 g
INACTIVE INGREDIENTS: PROPYLENE GLYCOL; GLYCERIN; WATER; UREA; POLYSORBATE 20; POTASSIUM IODIDE; BENZYL ALCOHOL; BORIC ACID

Forticept Anti-Itch Ear Drops - Medicated Otic Solution

Active Ingredient(s):

Hydrocortisone........1% (Anti-Itch)

Indications:

Helps relive itching associated with minor skin irritations, inflammation, and rashes.

Warnings:

For external use only / Not for human use
Keep out of reach of children - if swallowed, get medical help or contact a Poison Control Center right away.
When using this product - Avoid contact with eyes
Stop use and ask a veterinarian if condition worsens, symptoms persist for more than 7 days, or clear up and occur again with a few days, and do not begin use of any other hydrocortisone product unless you have asked a doctor.

Directions:

Pre-clean ear with Forticept® Antiseptic Ear Flush. Apply solution to the ear canal and with firm but gentle pressure, massage the base of the ear.

Storage:

Store at room temperature. Protect from freezing or excessive heat.

Inactive Ingredients:

Propylene Glycol, Glycerin, Water, Carbamide, Polysorbate 20, Povidone-iodine, Benzyl Alcohol, Boric Acid

Questions:

+1(470) 736-8166

Lidan, Inc., Kennesaw, GA 30152 USA

www.forticept.com